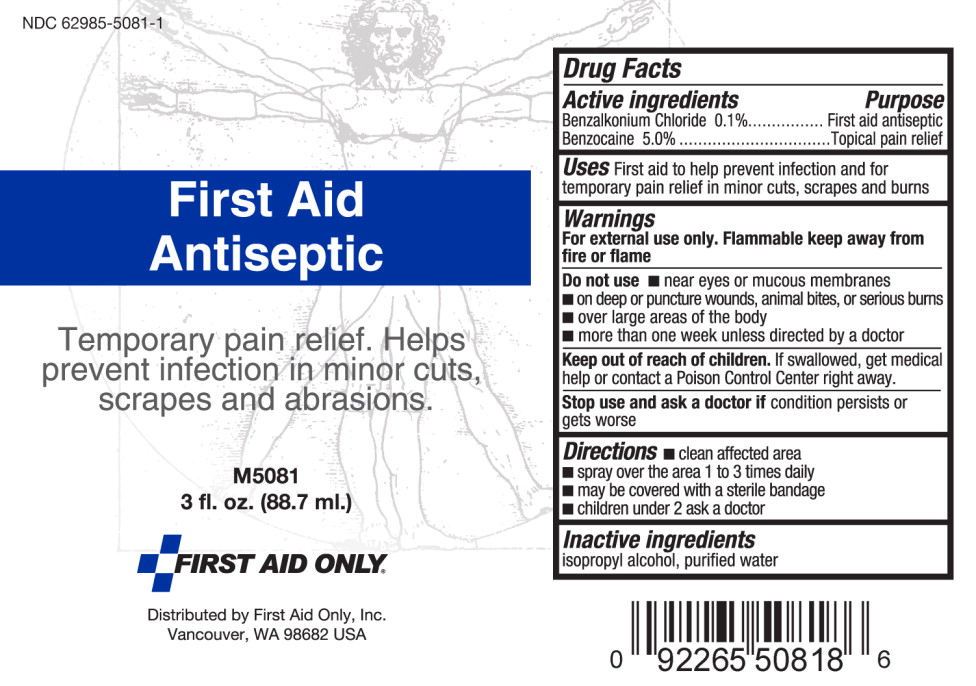 DRUG LABEL: First Aid Antiseptic
NDC: 62985-5081 | Form: SPRAY
Manufacturer: First Aid Only
Category: otc | Type: HUMAN OTC DRUG LABEL
Date: 20140813

ACTIVE INGREDIENTS: benzalkonium chloride 0.96 g/1 L; benzocaine 58.5 g/1 L
INACTIVE INGREDIENTS: isopropyl alcohol; water

Drug Facts

Active Ingredients

Benzalkonium Chloride 0.1%

Benzocaine 5.0%

Purpose

First Aid Antiseptic

Topical Pain Relief

Uses

First aid to help prevent infection and for temporary pain relief in minor cuts, scrapes and burns

Warnings

For external use only. Flammable keep away from fire or flame.

Do not use

- near eyes or mucous membranes
- on deep or puncture wounds, animal bites, or serious burns
- over large areas of the body
- more than one week unless directed by a doctor

Keep out of reach of children. If swallowed get medical help or contact a Poison Control Center right away.

Stop use and ask doctor if condition persists or gets worse

Directions

- clean affected and spray
- spray over the area 1 to 3 times daily
- may be covered with a sterile bandage
- children under 2 ask a doctor.

Inactive ingredients

isopropyl alcohol, purified water

PACKAGE LABEL

First Aid Antiseptic

Temporary pain relief. Helps prevent infection in minor cuts, scrapes and abrasions.

M5081

3 fl. oz (88.7 ml.)
----------
FIRST AID ONLY

Distributed by First Aid Only, Inc

Vancouver, WA 96882 USA